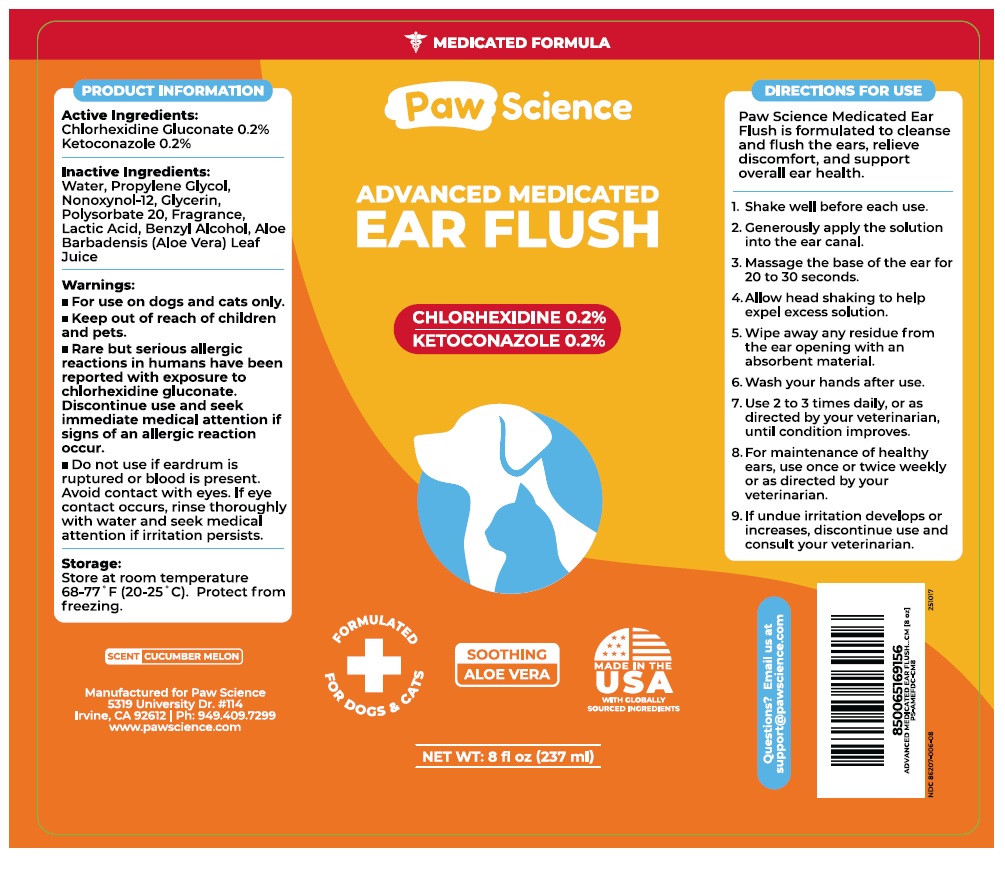 DRUG LABEL: Paw Science ADVANCED MEDICATED EAR FLUSH
NDC: 86207-006 | Form: SOLUTION
Manufacturer: Pet Science LLC
Category: animal | Type: OTC ANIMAL DRUG LABEL
Date: 20251103

ACTIVE INGREDIENTS: CHLORHEXIDINE GLUCONATE 2 mg/1 mL; KETOCONAZOLE 2 mg/1 mL
INACTIVE INGREDIENTS: WATER; PROPYLENE GLYCOL; NONOXYNOL-12; GLYCERIN; POLYSORBATE 20; LACTIC ACID, UNSPECIFIED FORM; BENZYL ALCOHOL; ALOE VERA LEAF JUICE

Paw Science ADVANCED MEDICATED EAR FLUSH

Active Ingredients:

Chlorhexidine Gluconate 0.2%
Ketoconazole 0.2%

Inactive Ingredients:

Water, Propylene Glycol, Nonoxynol-12, Glycerin, Polysorbate 20, Fragrance, Lactic Acid, Benzyl Alcohol, Aloe Barbadensis (Aloe Vera) Leaf Juice

Warnings:

• For use on dogs and cats only.
• Keep out of reach of children and pets.
• Rare but serious allergic reactions in humans have been reported with exposure to chlorhexidine gluconate. Discontinue use and seek immediate medical attention if signs of an allergic reaction occur.
• Do not use if eardrum is ruptured or blood is present. Avoid contact with eyes. If eye contact occurs, rinse thoroughly with water and seek medical attention if irritation persists.

Storage:

Store at room temperature 68–77° F (20–25° C). Protect from freezing.

DIRECTIONS FOR USE

Paw Science Medicated Ear Flush is formulated to cleanse and flush the ears, relieve discomfort, and support overall ear health.

1. Shake well before each use.
2. Generously apply the solution into the ear canal.
3. Massage the base of the ear for 20 to 30 seconds.
4. Allow head shaking to help expel excess solution.
5. Wipe away any residue from the ear opening with an absorbent material.
6. Wash your hands after use.
7. Use 2 to 3 times daily, or as directed by your veterinarian, until condition improves.
8. For maintenance of healthy ears, use once or twice weekly or as directed by your veterinarian.
9. If undue irritation develops or increases, discontinue use and consult your veterinarian.

MEDICATED FORMULA

FORMULATED FOR DOGS & CATS

SOOTHING ALOE VERA

MADE IN THE USA WITH GLOBALLY SOURCED INGREDIENTS

Questions? Email us at support@pawscience.com

SCENT CUCUMBER MELON

Manufactured for Paw Science
5319 University Dr. #114
Irvine, CA 92612 | Ph: 949.409.7299
www.pawscience.com